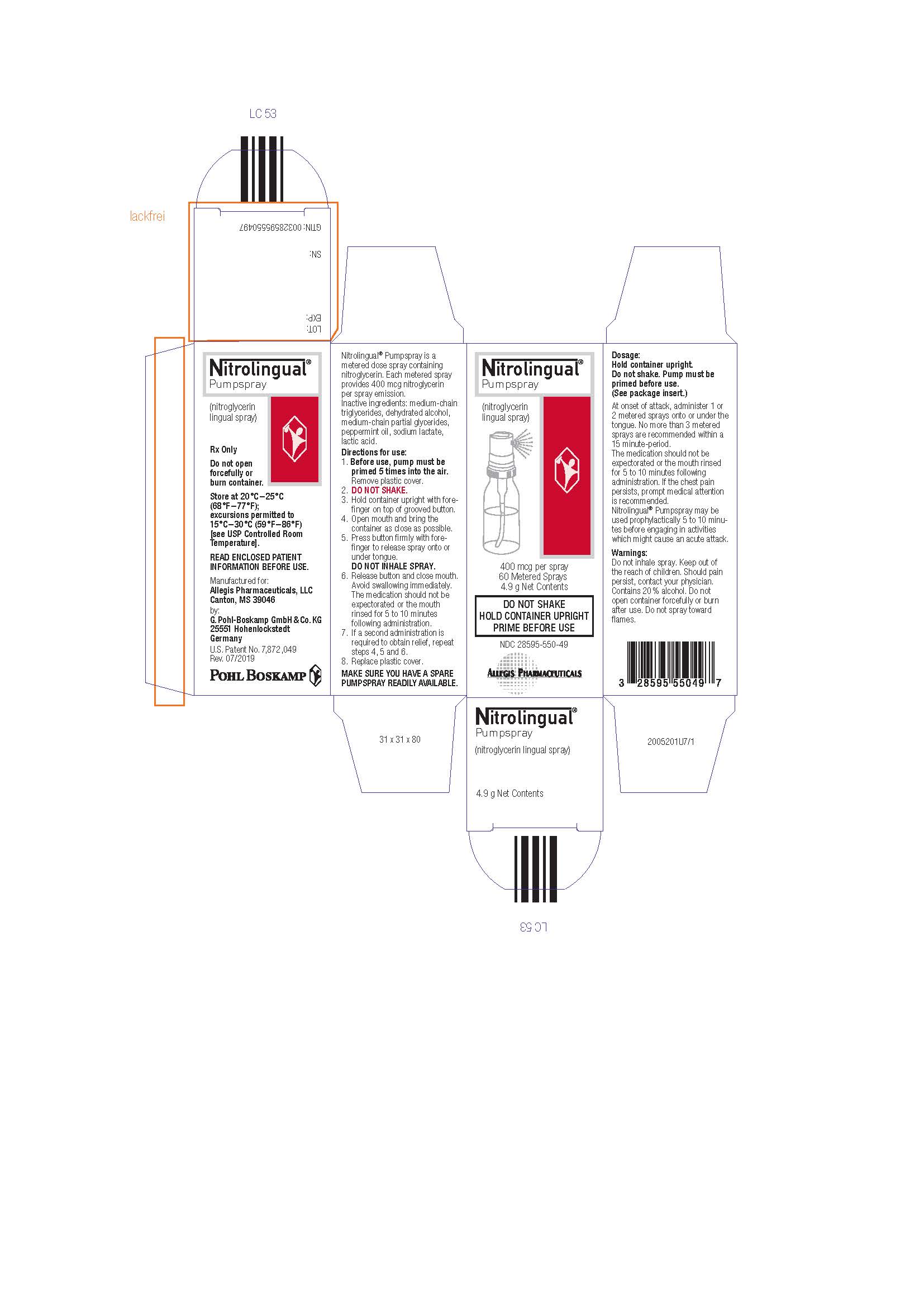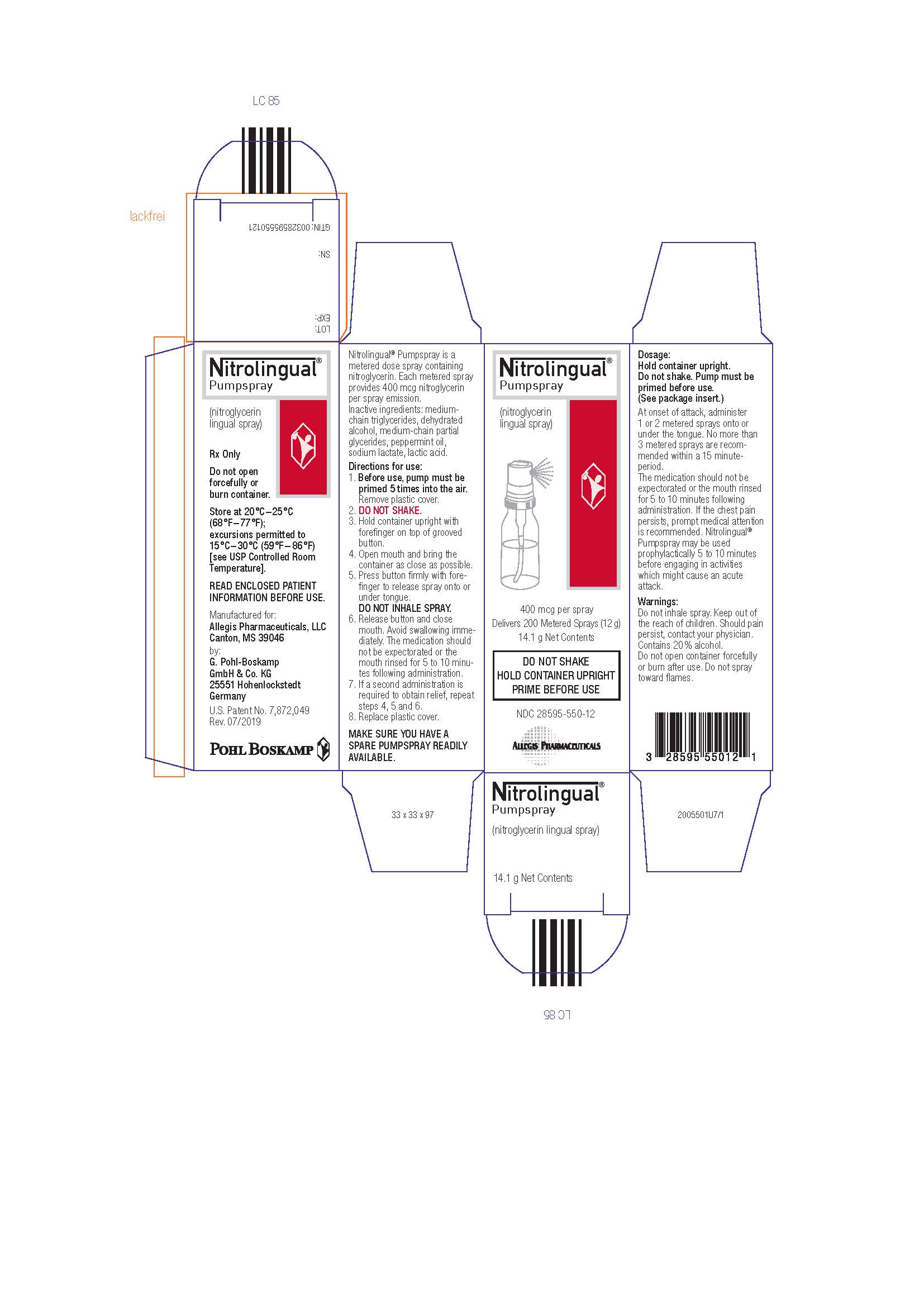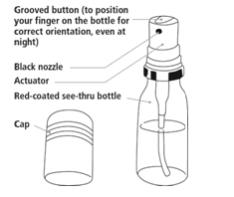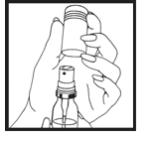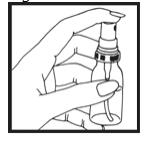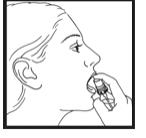 DRUG LABEL: NITROLINGUAL
NDC: 28595-550 | Form: SPRAY
Manufacturer: Allegis Pharmaceuticals, LLC
Category: prescription | Type: HUMAN PRESCRIPTION DRUG LABEL
Date: 20251217

ACTIVE INGREDIENTS: NITROGLYCERIN 400 ug/1 1
INACTIVE INGREDIENTS: MEDIUM-CHAIN TRIGLYCERIDES; ALCOHOL; PEPPERMINT OIL; SODIUM LACTATE; LACTIC ACID

HIGHLIGHTS OF PRESCRIBING INFORMATION

These highlights do not include all the information needed to use NITROLINGUAL® PUMPSPRAY safely and effectively. See full prescribing information for NITROLINGUAL PUMPSPRAY.
NITROLINGUAL® PUMPSPRAY (nitroglycerin) lingualspray
Initial U.S. Approval: 1997

1 INDICATIONS AND USAGE

Nitrolingual Pumpspray is a nitrate vasodilator indicated for acute relief of an attack or prophylaxis of angina pectoris due to coronary artery disease (1).

2 DOSAGE AND ADMINISTRATION

- At the onset of an attack, administer onto or under the tongue. Repeat every 5 minutes as needed (2.1).
- Do up to three metered sprays within a 15-minute period. If chest pain persists, advise prompt medical attention (2.1).
- May be used prophylactically 5 to 10 minutes prior to engaging in activities that might precipitate an acute attack (2.1).

3 DOSAGE FORMS AND STRENGTHS

Lingual spray, 400 mcg per spray, available in 60 or 200 metered sprays per container (3).

4 CONTRAINDICATIONS

- Use of phosphodiesterase type 5 (PDE-5) Inhibitors, such as avanafil, sildenafil, tadalafil, or vardenafil, or soluble guanylate cyclase (sGC) stimulator (riociguat). (4.1, 7.1)
- Severe anemia. (4.2)
- Increased intracranial pressure. (4.3)
- Hypersensitivity to Nitrolingual Pumpspray or to other nitrates or nitrites or any excipient. (4.4)

5 WARNINGS AND PRECAUTIONS

Tolerance:Excessive use may lead to tolerance. (5.1)

Hypotension:Severe hypotension may occur. (5.2)

6 ADVERSE REACTIONS

Most common adverse reactions occurring at a frequency greater than 2 % are headache, dizzinesss and paresthesia (6).

To report SUSPECTED ADVERSE REACTIONS, contact Allegis Pharmaceuticals, LLC at 1-866-633-9033 or FDA at 1-800-FDA-1088 or www.fda.gov/medwatch.

7 DRUG INTERACTIONS

- Antihypertensives: possible additive hypotensive effects. (7.2)
- Ergotamine: increased bioavailability of ergotamine. Avoid concomitant use (7.3)

FULL PRESCRIBING INFORMATION

1 INDICATIONS AND USAGE

Nitrolingual Pumpspray is indicated for acute relief of an attack or prophylaxis of angina pectoris due to coronary artery disease.

2 DOSAGE AND ADMINISTRATION

2.1 Recommended Dosage

Instruct the patient to administer one or two metered sprays (400 mcg of nitroglycerin per spray) at the onset of an attack onto or under the tongue. A spray may be repeated approximately every five minutes as needed. No more than three metered sprays are recommended within a 15-minute period. If the chest pain persists after a total ofthreesprays, advise prompt medical attention. Nitrolingual Pumpspray may be used prophylactically 5 to 10 minutes prior to engaging in activities that might precipitate an acute attack.

2.2 Priming

The pump must be primed prior to the first use. Each metered spray of Nitrolingual Pumpspray delivers 48 mg of solution containing 400 mcg of nitroglycerin after an initial priming of five sprays. It will remain adequately primed for 6 weeks. If the product is not used within 6 weeks it can be adequately re-primed with one spray. If the product is not used within 3 months it can be adequately re-primed with up to five sprays. There are 60 or 200 metered sprays per bottle. The total number of available doses is dependent, however, on the number of sprays per use (1 or 2 sprays), and the frequency of priming.

2.3 Administration

Instruct patients that during administration, the patient should rest, ideally in the sitting position. Hold the container vertically with the valve head uppermost and the spray orifice as close to the mouth as possible. Spray the dose preferably onto or under the tongue by pressing the grooved-button firmly and the mouth closed immediately after each dose. THE SPRAY SHOULD NOT BE INHALED. The medication should not be expectorated or the mouth rinsed for 5 to 10 minutes following administration. Instruct patients to familiarize themselves with the position of the spray orifice, which can be identified by the finger rest on top of the valve, in order to facilitate orientation for administration at night [see Patient Information (17)].

The amount of liquid remaining in the container should be checked periodically. The transparent container can be used for continuous monitoring of the consumption. With the container upright and level, check to be sure the end of the center tube extends below the level of the liquid. Once fluid falls below the level of the center tube, remaining sprays will not deliver intended dose.

3 DOSAGE FORMS AND STRENGTHS

Lingual spray, 400 mcg per spray available in either 60 or 200 metered sprays per container.

4 CONTRAINDICATIONS

4.1 PDE-5-InhibitorsandsGC-Stimulators

Do not use Nitrolingual Pumpspray in patients who are taking PDE-5-Inhibitors, such as avanafil, sildenafil, tadalafil, or vardenafil. Concomitant use can cause severe hypotension, syncope, or myocardial ischemia [see Drug Interactions (7.1)].

Do not use Nitrolingual Pumpspray in patients who are taking soluble guanylate cyclase (sGC) stimulators, such as riociguat. Concomitant use can cause hypotension.

4.2 Severe Anemia

Nitrolingual Pumpspray is contraindicated in patients with severe anemia (large doses of nitroglycerin may cause oxidation of hemoglobin to methemoglobin and could exacerbate anemia).

4.3 Increased Intracranial Pressure

Nitrolingual Pumpspray may precipitate or aggravate increased intracranial pressure and thus should not be used in patients with possible increased intracranial pressure (e. g. cerebral hemorrhage or traumatic brain injury).

4.4 Hypersensitivity

Nitrolingual Pumpspray is contraindicated in patients who are allergic to nitroglycerin, other nitrates or nitrites or any excipient.

4.5 Circulatory Failure and Shock

Nitrolingual Pumpspray is contraindicated in patients with acute circulatory failure or shock.

5 WARNINGS AND PRECAUTIONS

5.1 Tolerance

Excessive use may lead to the development of tolerance. Only the smallest number of doses required for effective relief of the acute angina attack should be used [see Dosage and Administration (2.1)].

5.2 Hypotension

Severe hypotension, particularly with upright posture, may occur even with small doses of nitroglycerin particularly in patients with constrictive pericarditis, aortic or mitral stenosis, patients who may be volume-depleted, or are already hypotensive. Hypotension induced by nitroglycerin may be accompanied by paradoxical bradycardia and increased angina pectoris. Symptoms of severe hypotension (nausea, vomiting, weakness, pallor, perspiration and collapse/syncope) may occur even with therapeutic doses.

5.3 Hypertrophic Obstructive Cardiomyopathy

Nitrate therapy may aggravate the angina caused by hypertrophic obstructive cardiomyopathy.

5.4 Headache

Nitroglycerin produces dose-related headaches, especially at the start of nitroglycerin therapy, which may be severe and persistent but usually subside with continued use.

6 ADVERSE REACTIONS

6.1 Clinical Trials Experience

Because clinical trials are conducted under widely varying conditions, adverse reaction rates observed in the clinical trials of a drug cannot be directly compared to rates in the clinical trials of another drug and may not reflect the rates observed in clinical practice.

Adverse reactions occurring at a frequency greater than 2 % and greater than placebo included: headache, dizziness, and paresthesia.

6.2 Postmarketing Experience

The following adverse reactions have been identified during post-approval use of Nitrolingual Pumpspray and other nitroglycerin drugs. Because these reactions are reported voluntarily from a population of uncertain size, it is not always possible to estimate their frequency reliably or establish a causal relationship to drug exposure.

Neurologic:weakness, drowsiness
Dermatologic:cutaneous vasodilation, flushing, drug rash, exfoliative dermatitits
Gastrointestinal:nausea, vomiting
Respiratory:transient hypoxemia
Cardiovascular: tachycardia

7 DRUG INTERACTIONS

7.1 PDE-5-InhibitorsandsGC-Stimulators

Nitrolingual Pumpspray is contraindicated in patients who are using a selective inhibitor of cyclic guanosine monophosphate (cGMP)-specific phosphodiesterase type 5 (PDE-5). PDE-5-Inhibitors such as avanafil, sildenafil, vardenafil, and tadalafil have been shown to potentiate the hypotensive effects of organic nitrates.

Nitrolingual Pumpspray is contraindicated in patients who are taking soluble guanylate cyclase (sGC) stimulators. Concomitant use can cause hypotension.

The time course and dose dependence of these interactions have not been studied, and use within a few days of one another is not recommended. Appropriate supportive care for the severe hypotension has not been studied, but it seems reasonable to treat this as a nitrate overdose, with elevation of the extremities and with central volume expansion.

7.2 Antihypertensives

Patients receiving antihypertensive drugs, beta-adrenergic blockers, and nitrates should be observed for possible additive hypotensive effects. Marked orthostatic hypotension has been reported when calcium channel blockers and organic nitrates were used concomitantly.

Beta-adrenergic blockers blunt the reflex tachycardia produced by nitroglycerin without preventing its hypotensive effects. If beta-blockers are used with nitroglycerin in patients with angina pectoris, additional hypotensive effects may occur.

7.3 Ergotamine

Oral administration of nitroglycerin markedly decreases the first-pass metabolism of dihydroergotamine and subsequently increases its oral bioavailability. Ergotamine is known to precipitate angina pectoris. Therefore, patients receiving sublingual nitroglycerin should avoid ergotamine and related drugs or be monitored for symptoms of ergotism if this is not possible.

8 USE IN SPECIFIC POPULATIONS

8.1 Pregnancy

Risk summary
Limited published data on the use of nitroglycerin are insufficient to determine a drug associated risk of major birth defects or miscarriage. In animal reproduction studies, there were no adverse developmental effects when nitroglycerin was administered intravenously to rabbits or intraperitoneally to rats during organogenesis at doses greater than 64-times the human dose [see Data].

The estimated background risk of major birth defects and miscarriage for the indicated population is unknown. In the U.S. general population, the estimated background risk of major birth defects and miscarriage in clinically recognized pregnancies is 2 – 4% and 15 – 20%, respectively.

Data
Animal Data
No embryotoxic or postnatal development effects were observed with transdermal application in pregnant rabbits and rats at doses up to 240 mg/kg/day for 13 days, at intraperitoneal doses in pregnant rats up to 20 mg/kg/day for 11 days, and at intravenous doses in pregnant rabbits up to 4 mg/kg/day for 13 days.

8.2 Lactation

Risk summary
Sublingual nitroglycerin has not been studied in lactating women. It is not known if nitroglycerin is present in human milk or if nitroglycerin has effects on milk production. The developmental and health benefits of breastfeeding should be considered along with the mother’s clinical need for nitroglycerin and any potential adverse effects on the breastfed child from nitroglycerin or from the underlying maternal condition.

8.4 Pediatric Use

Safety and effectiveness of nitroglycerin in pediatric patients have not been established.

8.5 Geriatric Use

Clinical studies did not include sufficient numbers of subjects aged 65 and over to determine whether they respond differently from younger subjects. Other reported clinical experience has not identified differences in responses between elderly (greater than or equal to 65 years) and younger (less than 65 years) patients. In general, dose selection for an elderly patient should start at the low end of the dosing range, reflecting the greater frequency of decreased hepatic, renal, or cardiac function, and of concomitant disease or other drug therapy.

10 OVERDOSAGE

10.1 Signs and Symptoms, Methemoglobinemia

Nitrate overdosage may result in: severe hypotension, persistent throbbing headache, vertigo, palpitation, visual disturbance, flushing and perspiring skin (later becoming cold and cyanotic), nausea and vomiting (possibly with colic and even bloody diarrhea), syncope (especially in the upright posture), methemoglobinemia with cyanosis and anorexia, initial hyperpnea, dyspnea and slow breathing, slow pulse (dicrotic and intermittent), heart block, increased intracranial pressure with cerebral symptoms of confusion and moderate fever, paralysis and coma followed by clonic convulsions, and possibly death due to circulatory collapse.

Case reports of clinically significant methemoglobinemia are rare at conventional doses of organic nitrates. The formation of methemoglobin is dose-related and in the case of genetic abnormalities of hemoglobin that favor methemoglobin formation, even conventional doses of organic nitrates could produce harmful concentrations of methemoglobin.

10.2 Treatment of Overdosage

As hypotension associated with nitroglycerin overdose is the result of venodilatation and arterial hypovolemia, prudent therapy in this situation should be directed toward increase in central fluid volume. No specific antagonist to the vasodilator effects of nitroglycerin is known. Keep the patient recumbent in a shock position and comfortably warm. Passive movement of the extremities may aid venous return. Intravenous infusion of normal saline or similar fluid may also be necessary. Administer oxygen and artificial ventilation, if necessary. If methemoglobinemia is present, administration of methylene blue (1 % solution), 1 – 2 mg per kilogram of body weight intravenously, may be required unless the patient is known to have G-6-PD deficiency. If an excessive quantity of Nitrolingual Pumpspray has been recently swallowed gastric lavage may be of use.

As epinephrine is ineffective in reversing the severe hypotensive events associated with overdosage, it is not recommended for resuscitation.

11 DESCRIPTION

Nitroglycerin, an organic nitrate, is a vasodilator which has effects on both arteries and veins. The chemical name for nitroglycerin is 1,2,3-propanetriol trinitrate (C3H5N3O9). The compound has a molecular weight of 227.09. The chemical structure is:

CH2–ONO2

|

CH–ONO2

|

CH2–ONO2

Nitrolingual Pumpspray (nitroglycerin lingual spray 400 mcg) is a metered dose spray containing nitroglycerin. This product delivers nitroglycerin (400 mcg per spray, 60 or 200 metered sprays) in the form of spray droplets onto or under the tongue. Inactive ingredients: medium-chain triglycerides, dehydrated alcohol, medium-chain partial glycerides, peppermint oil, sodium lactate, lactic acid.

12 CLINICAL PHARMACOLOGY

12.1 Mechanism of Action

Nitroglycerin forms free radical nitric oxide (NO), which activates guanylate cyclase, resulting in an increase of guanosine 3',5'-monophosphate (cyclic GMP) in smooth muscle and other tissues. This eventually leads to dephosphorylation of myosin light chains, which regulates the contractile state in smooth muscle and results in vasodilatation.

12.2 Pharmacodynamics

The principal pharmacological action of nitroglycerin is relaxation of vascular smooth muscle. Although venous effects predominate, nitroglycerin produces, in a dose-related manner, dilation of both arterial and venous beds. Dilation of the postcapillary vessels, including large veins, promotes peripheral pooling of blood, decreases venous return to the heart, and reduces left ventricular end-diastolic pressure (preload). Nitroglycerin also produces arteriolar relaxation, thereby reducing peripheral vascular resistance and arterial pressure (after load), and dilates large epicardial coronary arteries; however, the extent to which this latter effect contributes to the relief of exertional angina is unclear.

Therapeutic doses of nitroglycerin may reduce systolic, diastolic and mean arterial blood pressure. Effective coronary perfusion pressure is usually maintained, but can be compromised if blood pressure falls excessively or increased heart rate decreases diastolic filling time.

Elevated central venous and pulmonary capillary wedge pressures, and pulmonary and systemic vascular resistance are also reduced by nitroglycerin therapy. Heart rate is usually slightly increased, presumably a reflex response to the fall in blood pressure. Cardiac index may be increased, decreased, or unchanged. Myocardial oxygen consumption or demand (as measured by the pressure-rate product, tension-time index, and stroke-work index) is decreased and a more favorable supply-demand ratio can be achieved. Patients with elevated left ventricular filling pressure and increased systemic vascular resistance in association with a depressed cardiac index are likely to experience an improvement in cardiac index. In contrast, when filling pressures and cardiac index are normal, cardiac index may be slightly reduced following nitroglycerin administration.

12.3 Pharmacokinetics

A liver reductase enzyme is of primary importance in the metabolism of nitroglycerin to glycerol di- and mononitrate metabolites and ultimately to glycerol and organic nitrate. Known sites of extrahepatic metabolism include red blood cells and vascular walls. In addition to nitroglycerin, 2 major metabolites, 1,2- and 1,3-dinitroglycerin are found in plasma. The mean elimination half-life of both 1,2- and 1,3-dinitroglycerin is about 40 minutes. The 1,2- and 1,3-dinitroglycerin metabolites have been reported to possess some pharmacological activity, whereas the glycerol mononitrate metabolites of nitroglycerin are essentially inactive. Higher plasma concentrations of the dinitro metabolites, with their nearly 8-fold longer elimination half-lives, may contribute significantly to the duration of pharmacologic effect.

In a pharmacokinetic study when a single 0.8 mg dose of Nitrolingual Pumpspray was administered to healthy volunteers (n = 24), the mean Cmaxand tmaxwere 1,041 pg/ml and 7.5 minutes, respectively. Additionally, in these subjects the mean area under the curve (AUC) was 12,769 pg/ml * min.

The volume of distribution of nitroglycerin following intravenous administration is 3.3 L/kg.

Drug interactions

Aspirin: Coadministration of nitroglycerin with high dose aspirin (1000 mg) results in increased exposure to nitroglycerin. The vasodilatory and hemodynamic effects of nitroglycerin may be enhanced by concomitant administration of nitroglycerin with high dose aspirin.

Tissue-type plasminogen activator (t-PA): Concomitant administration of t-PA and intravenous nitroglycerin has been shown to reduce plasma levels of t-PA and its thrombolytic effect.

13 NONCLINICAL TOXICOLOGY

13.1 Carcinogenesis, Mutagenesis, Impairment of Fertility

Animal carcinogenesis studies with sublingual nitroglycerin have not been performed.

Rats receiving up to 434 mg/kg/day of dietary nitroglycerin for 2 years developed dose-related fibrotic and neoplastic changes in liver, including carcinomas, and interstitial cell tumors in testes. At high dose, the incidences of hepatocellular carcinomas in both sexes were 52 % vs. 0 % in controls, and incidences of testicular tumors were 52 % vs. 8 % in controls. Lifetime dietary administration of up to 1058 mg/kg/day of nitroglycerin was not tumorigenic in mice.

Nitroglycerin was weakly mutagenic in Ames tests performed in two different laboratories. There was no evidence of mutagenicity in an in vivodominant lethal assay with male rats treated with doses up to about 363 mg/kg/day, p.o., or in in vitrocytogenic tests in rat and dog tissues and for chromosomal aberration in Chinese hamster ovary cells.

In a three-generation reproduction study, rats received dietary nitroglycerin at doses up to about 434 mg/kg/day for six months prior to mating of the F0generation with treatment continuing through successive F1and F2generations. The high dose was associated with decreased feed intake and body weight gain in both sexes at all matings. No specific effect on the fertility of the F0generation was seen. Infertility noted in subsequent generations, however, was attributed to increased interstitial cell tissue and aspermatogenesis in the high- dose males. In this three-generation study there was no clear evidence of teratogenicity.

14 CLINICAL STUDIES

In a randomized, double-blind single-dose, 5-period cross-over study in 51 patients with exertional angina pectoris significant dose-related increases in exercise tolerance, time to onset of angina and ST-segment depression were seen following doses of 0.2, 0.4, 0.8 and 1.6 mg of nitroglycerin delivered by metered pumpspray as compared to placebo.

The drug showed a profile of mild to moderate adverse events.

16 HOW SUPPLIED/STORAGE AND HANDLING

Each box of Nitrolingual Pumpspray contains one glass bottle coated with red transparent plastic which assists in containing the glass and medication should the bottle be shattered. Each bottle contains 4.9 g or 14.1 g (Net Contents) of nitroglycerin lingual spray which will deliver 60 or 200 metered sprays containing 400 mcg of nitroglycerin per spray after priming.

Nitrolingual Pumpspray is available as:

- 60-dose (4.9 g) single bottle NDC 28595-550-49
- 200-dose (14.1 g) single bottle NDC 28595-550-12

Store at 20°C - 25°C (68°F - 77°F); excursions permitted to 15°C - 30°C (59°F - 86°F) [see USP Controlled Room Temperature].

Note: Nitrolingual Pumpspray contains 20 % alcohol. Do not forcefully open or burn container after use. Do not spray toward flames.

Rx Only.

17 PATIENT COUNSELING INFORMATION

Advise the patient to read the FDA-approved patient labeling (Instructions for Use)

The following trademarks are either registered trademarks or trademarks of Pohl-Boskamp in the United States and/or other countries: Pohl-Boskamp word mark; Pohl-Boskamp logo; Nitrolingual word mark; Nitrolingual Pumpspray shapes, Nitrolingual Pumpspray colors.

U.S. Patent No. 7,872,049

Manufactured for
Allegis Pharmaceuticals, LLC Canton, MS 39046
by G. Pohl-Boskamp GmbH & Co. KG,
25551 Hohenlockstedt, Germany.

PATIENT INFORMATION

Instructions for Use
Nitrolingual® Pumpspray (nī-trō-ling´gwal)
(nitroglycerin)
lingualspray

Read this Instructions for Use before you start using Nitrolingual Pumpspray and each time you get your prescription refilled. There may be new information. This information does not take the place of talking to your healthcare provider about your medical condition or your treatment.

Important information:

- Nitrolingual Pumpspray is for use ontoor under the tongue.Do not inhale Nitrolingual Pumpspray.
- A dose of Nitrolingual Pumpspray may be either 1 or 2 sprays. Follow your healthcare provider’s instructions about how many sprays you should use for each dose. Doses should be separated by approximately 5 minutes.
- You should not use more than 3 sprays of Nitrolingual Pumpspray within 15 minutes.
- Get emergency medical help right away if you still have chest pain after using a total of 3 sprays of Nitrolingual Pumpspray.

Nitrolingual Pumpspray parts:

Figure A

Howshould Iuse Nitrolingual Pumpspray?

- It is best to use Nitrolingual Pumpspray while you are resting and in a sitting position.
- Do notshake the Nitrolingual Pumpspray container.

Priming Nitrolingual Pumpspray:

Before you use Nitrolingual Pumpspray for the first time, you must prime it. To prime your Nitrolingual Pumpspray, follow the steps below:

Step 1. Remove the plastic cap from the container. (See Figure B)

Figure B

Step 2. Hold the container upright and facing away from yourself and others. Press down on the top of the grooved button 5 times. (See Figure C)

Figure C

- Your Nitrolingual Pumpspray is now primed. You are ready to give your first dose.
- If you do not use your Nitrolingual Pumpspray within 6 weeks, you will need to prime it again by pressing down on the top of the grooved button 1 time.
- If you do not use your Nitrolingual Pumpspray within 3 months, you will need to re-prime it by pressing down on the top of the grooved button up to 5 times.

Giving a dose of Nitrolingual Pumpspray:

Step 3. Hold your Nitrolingual Pumpspray container upright with your index finger on top of the grooved button.

Step 4. Open your mouth and bring the Nitrolingual Pumpspray container as close to your mouth as possible.

Step 5. Press down on the top of the grooved button firmly with your index finger to release the spray onto or under your tongue. (See Figure D). The grooved button can help you make sure the canister is turned to the correct position if you are administering the spray in the dark.

Figure D

Step 6. Release the grooved button and close your mouth right away. Avoid swallowing right after using Nitrolingual Pumpspray. Do not spit out Nitrolingual Pumpspray or rinse your mouth for 5 to 10 minutes after using Nitrolingual Pumpspray.

Step 7. If a second dose of Nitrolingual Pumpspray is needed, repeat Steps 3 through 6 above.

Step 8. Replace the plastic cap.

Check the level of the fluid in your Nitrolingual Pumpspray container regularly.

- Check the container in an upright position.
- The end of the center tube should be covered by the fluid in the Nitrolingual Pumpspray container. If the level of the fluid falls below the end of the center tube, sprays will not provide enough Nitrolingual Pumpspray.
- Replace your Nitrolingual Pumpspray container before the fluid level falls below the end of the center tube.

How should I store Nitrolingual Pumpspray?

- Store Nitrolingual Pumpspray at room temperature between 68°F - 77°F (20°C - 25°C).
- Do not forcefully open or burn the Nitrolingual Pumpspray container after use.
- Do not spray Nitrolingual Pumpspray toward flames.

Keep Nitrolingual Pumpspray and all medicines out of the reach of children.

This Instructions for Use has been approved by the U.S. Food and Drug Administration.

Manufactured for Allegis Pharmaceuticals, LLC Canton, MS 39046

by G. Pohl-Boskamp GmbH & Co. KG, 25551 Hohenlockstedt, Germany.

Revised: 07/2019

The following trademarks are either registered trademarks or trademarks of Pohl-Boskamp in the United States and / or other countries: Pohl-Boskamp word mark; Pohl-Boskamp logo; Nitrolingual word mark; Nitrolingual Pumpspray shapes, Nitrolingual Pumpspray colors.

PACKAGE LABEL

PRINCIPAL DISPLAY PANEL
Nitrolingual
Pumpspray
Rx Only
400 Mcg per spray
200 Metered Sprays
14.1 g Net Contents

PACKAGE LABEL

PRINCIPAL DISPLAY PANEL
Nitrolingual
Pumpspray
Rx Only
400 Mcg per spray
60 Metered Sprays
4.9 g Net Contents